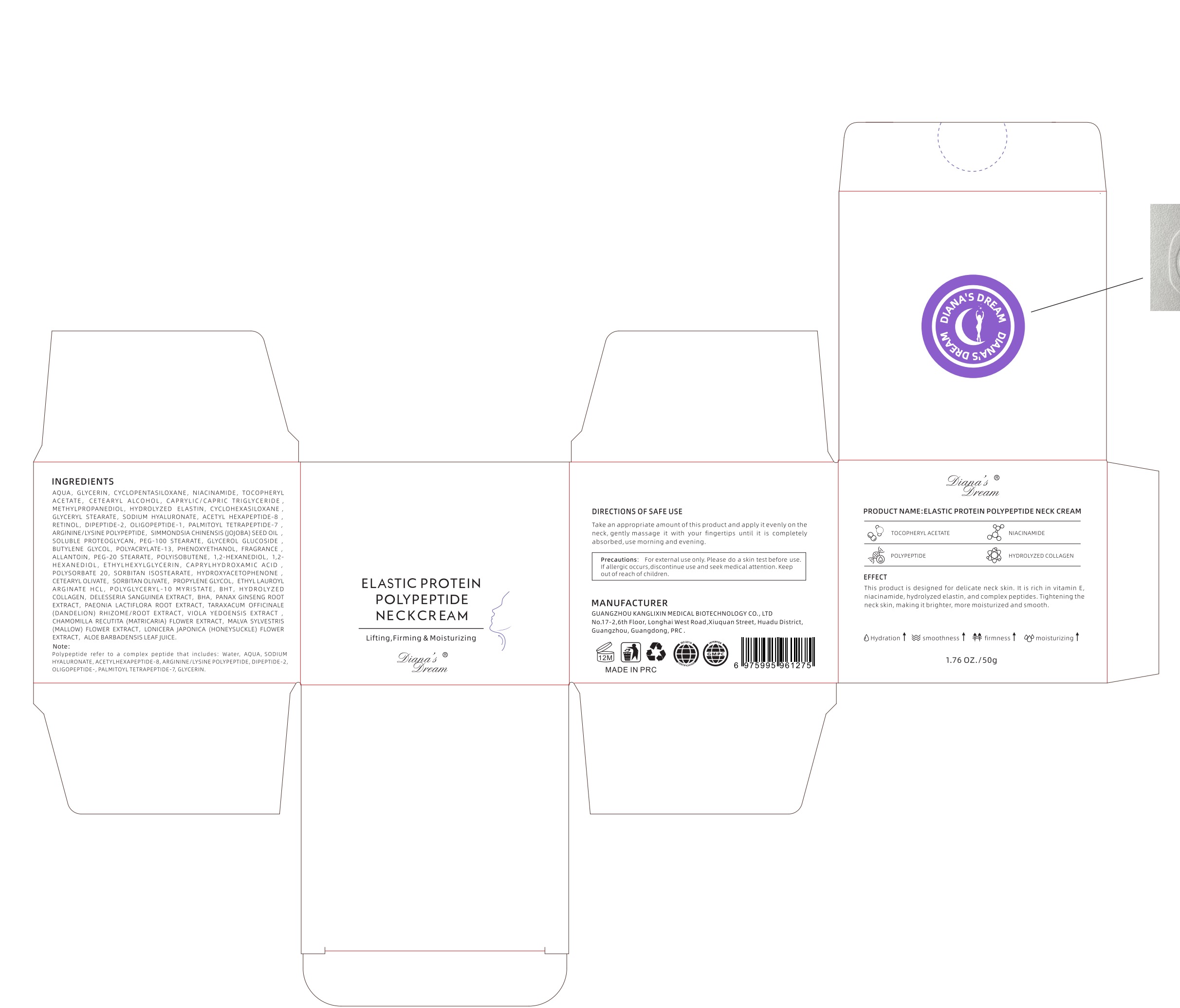 DRUG LABEL: Dianas Dream
NDC: 84854-003 | Form: CREAM
Manufacturer: Guangzhou Kanglixin Medicine Biotechnology Co., Ltd.
Category: otc | Type: HUMAN OTC DRUG LABEL
Date: 20241117

ACTIVE INGREDIENTS: GLYCERIN 2 g/2 cm2
INACTIVE INGREDIENTS: CYCLOPENTASILOXANE; CETEARYL ALCOHOL; CYCLOHEXASILOXANE; WATER; NIACINAMIDE; CAPRYLIC/CAPRIC TRIGLYCERIDE; METHYLPROPANEDIOL; GLYCERYL STEARATE; HYDROLYZED ELASTIN

inactive

AQUA

CYCLOPENTASILOXANE

NIACINAMIDE

TOCOPHERYL ACETATE

CETEARYL ALCOHOL

CAPRYLIC/CAPRIC TRIGLYCERIDE

METHYLPROPANEDIOL

HYDROLYZED ELASTIN

CYCLOHEXASILOXANE

GLYCERYL STEARATE

SODIUM HYALURONATE

ACETYL HEXAPEPTIDE-8

RETINOL

DIPEPTIDE-2

OLIGOPEPTIDE-1

PALMITOYL TETRAPEPTIDE-7

ARGININE/LYSINE POLYPEPTIDE

SIMMONDSIA CHINENSIS (JOJOBA) SEED OIL

SOLUBLE PROTEOGLYCAN

PEG-100 STEARATE

GLYCEROL GLUCOSIDE

BUTYLENE GLYCOL

POLYACRYLATE-13

PHENOXYETHANOL

FRAGRANCE

ALLANTOIN

PEG-20 STEARATE

POLYISOBUTENE

1,2-HEXANEDIOL

1,2-HEXANEDIOL

ETHYLHEXYLGLYCERIN

CAPRYLHYDROXAMIC ACID

POLYSORBATE 20

SORBITAN ISOSTEARATE

HYDROXYACETOPHENONE

CETEARYL OLIVATE

SORBITAN OLIVATE

PROPYLENE GLYCOL

ETHYL LAUROYL ARGINATE HCL

POLYGLYCERYL-10 MYRISTATE

BHT

HYDROLYZED COLLAGEN

DELESSERIA SANGUINEA EXTRACT

BHA

PANAX GINSENG ROOT EXTRACT

PAEONIA LACTIFLORA ROOT EXTRACT

TARAXACUM OFFICINALE (DANDELION) RHIZOME/ROOT EXTRACT

VIOLA YEDOENSIS EXTRACT

CHAMOMILLA RECUTITA (MATRICARIA) FLOWER EXTRACT

MALVA SYLVESTRIS (MALLOW) FLOWER EXTRACT

LONICERA JAPONICA (HONEYSUCKLE) FLOWER EXTRACT

ALOE BARBADENSIS LEAF JUICE

Purpose

This product is designed for delicate neck skin. lt is rich in vitamin E.niacinamide, hydrolyzed elastin,and complex peptides. Tightening theneck skin, makingit brighter, more moisturized and smooth.

Warning

for externaluse only. Please do a skin test before useIfallergic occurs,discontinue use and seek medicalattention. Keepoutofreach of children.

information

for externaluse only. Please do a skin test before useIfallergic occurs,discontinue use and seek medicalattention. Keepoutofreach of children.

stop to use

for externaluse only. Please do a skin test before useIfallergic occurs,discontinue use and seek medicalattention. Keepoutofreach of children.

when

When use on children,adulit,su-pervisionis required*When body tempera-ture over 39c seek medical advice

Storage

Storage: Store at room temperature andaway from sunlight and out of children

how to use

Take an appropriate amount of this product and apply it evenly on theneck,gently massage it with your fingertips until it is completelyabsorbed,use morning and evening.

Dosagee

2g one time

PACKAGE LABEL

INGREDIENTSYUCCADMC TAOYCENDEAetet cnemy tonatc HYDROLYZED ELASTICYCLOHEXASILOXREYCEOL, OUEDMDE. S OLGOPEPNDE , PE, MYOYL TERADEPHDE ?WANO CPGS0 SHAagOXYETHANOL, FRAGRANCEPOLYISOBUTENE, 1,2-HEXANEDIOL, HEXANEDIOL, ETHYLHEXYLGLYCERIN, CAPRYLHYDROXAMIC ACIPOLYSORBATE 20, SORBTTAN ISOSEROP, FVEROXOCERYL-T0 MYRISTATE, BHT, HYDROLYZEARGINATE HCCOLLAGEN, DELESSERIA SANGUINEA EXTRACT, BHA, PANAX GINSENG ROOLA VEDOENSIS EXTRAMOW EA NEGR EN WA LONGRAONANEA MON NSUY B YOWEXTRACT, ALOE BARBADENSIS LEAFJUICEPOND NNS EAC O SEADENDES ARG UNE NSWE WOEHDE UN ODE 2
AOETMLHEMAPEFADESO, AROTGNETRPNN
ELASTIC PROTEINPOLYPEPTIDENECKCREAM
Lifting,Firming & MoisturizingInga,@Dyeam
DIRECTIONS OF SAFE USEhed aany nssnce i mnh you nngetas nnvtis cownetoduct and applyit evenly on thuau ad eounueneneee oesten eonee e
MANUFACTURERICAL BIOTECHNOLOGY CO.. LT!eet Huadu DistricMADE IN PRCE
OionaseCreamPRODUCT NAME:ELASTIC PROTEIN POLYPEPTIDE NECK CREAMQTOCOPHERYLACETATE
ONACNAMDE
OPOLPEPTIDE
HYDROLYZED COLLAGEN
EFFECTThis product is designed for delicate neck skin. it is rich in vitamin tmore moiouneupept des. tightening theneckskn, makno nb onee no,
OHydration fsmoothnesst # firmnesst moisturizing t
1.76 0Z./50g